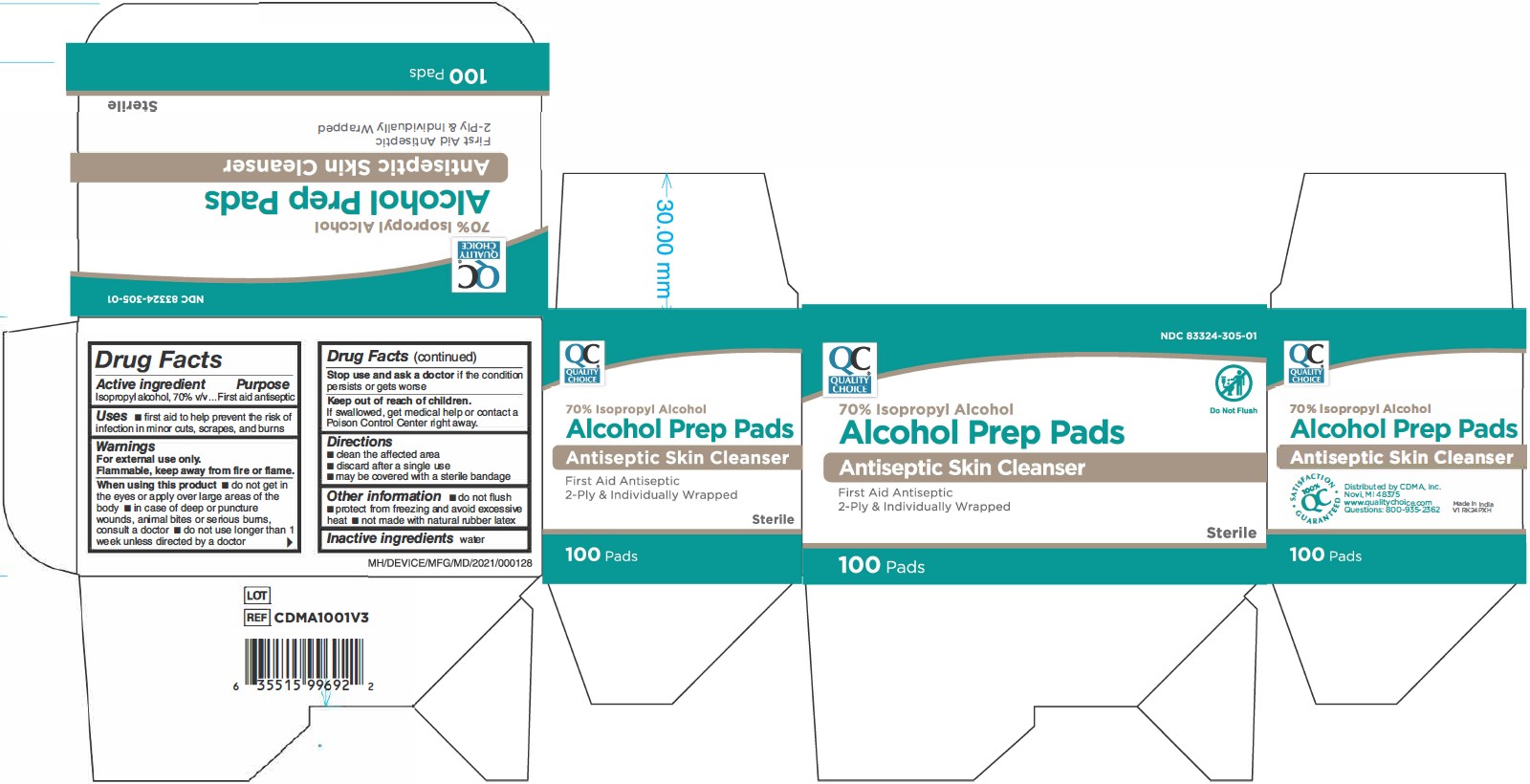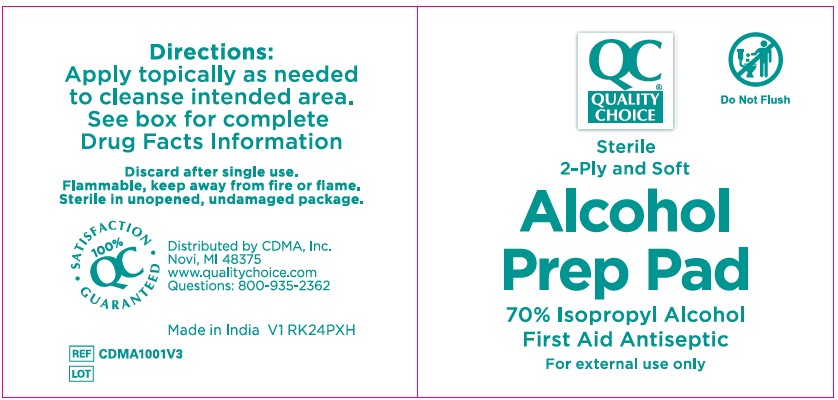 DRUG LABEL: Chain Drug Marketing Association, Inc.
NDC: 83324-305 | Form: CLOTH
Manufacturer: Chain Drug Marketing Association Inc.
Category: otc | Type: HUMAN OTC DRUG LABEL
Date: 20250822

ACTIVE INGREDIENTS: ISOPROPYL ALCOHOL 70 mL/100 mL
INACTIVE INGREDIENTS: WATER

83324-305 CDMA 70% IPA Prep Pads

Active ingredient

Isopropyl alcohol, 70% v/v

Purpose

First aid antiseptic

Uses

- first aid to help prevent the risk of infection in minor cuts, scrapes, and burns

Warnings

For external use only.

Flammable, keep away from fire or flame.

When using this product

- do not get in the eyes or apply over large areas of the body
- in case of deep or puncture wounds, animal bites or serious burns, consult a doctor
- do not use longer than 1 week unless directed by a doctor

Stop use and ask a doctor

if the condition persists or gets worse

Keep out of reach of children.

If swallowed, get medical help or contact a Poison Control Center right away.

Directions

- clean the affected area
- discard after a single use
- may be covered with a sterile bandage

Other information

- do not flush
- protect from freezing and avoid excessive heat
- not made with natural rubber latex

Inactive ingredients

water

Manufacturing Information

Distributed by:
C.D.M.A., Inc.©

43157 W 9 Mile Rd, Novi, MI 48375 USA

www.qualitychoice.com

248-449-9300

Packaged in China

Products of Taiwan

REF: CDMA1001V2

V2 RE24LPD